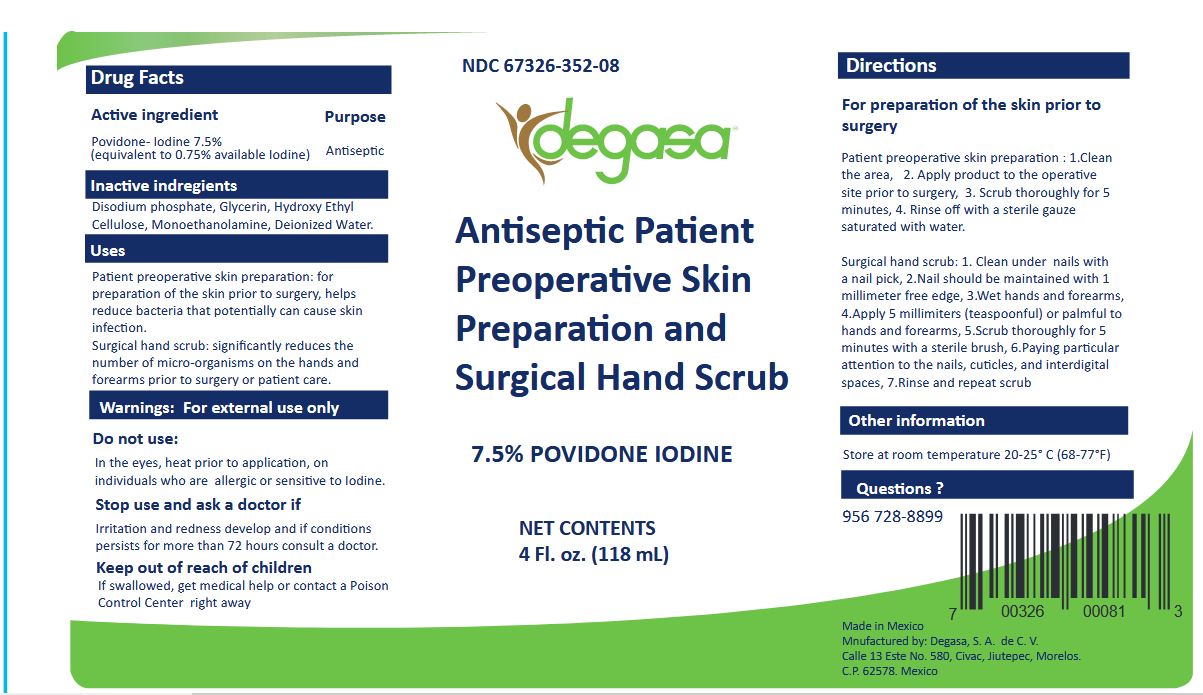 DRUG LABEL: Antiseptic Patient Preoperative Skin Preparation and Surgical Hand Scrub
NDC: 67326-352 | Form: SOLUTION
Manufacturer: Degasa SA De CV
Category: otc | Type: HUMAN OTC DRUG LABEL
Date: 20231105

ACTIVE INGREDIENTS: POVIDONE-IODINE 75 mg/1 mL
INACTIVE INGREDIENTS: SODIUM PHOSPHATE, DIBASIC, ANHYDROUS; GLYCERIN; MONOETHANOLAMINE; WATER

degasa Antiseptic Patient Preoperative Skin Preparation and Surgical Hand Scrub Povidone Iodine 7.5%

Active Ingredient

Povidone Iodine 7.5%

Purpose

Antiseptic

Uses

Patient preoperative skin preparation:

Surgical hand scrub:

- For preparation of the skin prior to surgery
- Helps reduce bacteria that potentially can cause skin infection

- Significantyl reduces the number of micro-organisms on the hands and forearms prior to surgery or patient care

WARNINGS: For External Use Only

Do not use

Stop use and ask a doctor if

- In the eyes
- Heat prior to application
- On individuals who are allergic or sensitive to Iodine

- Irritation and redness develop
- If condition persists for more than 72 hous consult a doctor

Keep out of reach of children

If swallowed, get medical help or contact a Poison Control Center right away

Directions

Patient preoperative skin preparation:

Surgical hand scrub:

- Clean the area
- Apply product to the operative site prior to surgery
- Scrub thoroughly for 5 minutes
- Rinse off with a sterile gauze saturated with water

- Clean under nails with a nail pick. Nail should be maintained with a 1 millimeter free edge
- Wet hands and forearms
- Apply 5 millileters (teaspoonful) or palmfull to hands and forearms
- Scub thoroughly for 5 minutes with a sterile brush
- Paying particular attention to the nails, cuticles, and interdigital spaces
- Rinse and repeat scrub

Other information

Store at room temperature 20-25°C (68-77°F)

Inactive Ingredients

Disodium Phosphate, Glycerin, Hidroxyethylcellulose, Monoethanolamine, Dionized Water